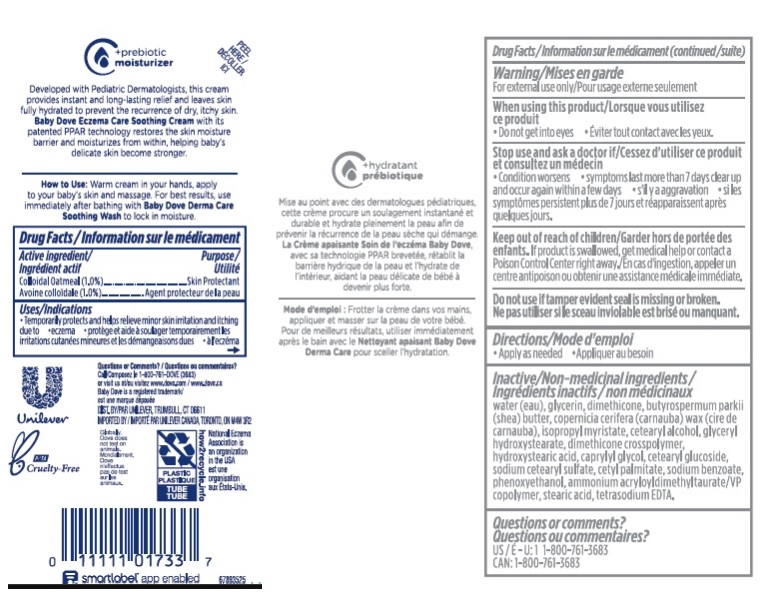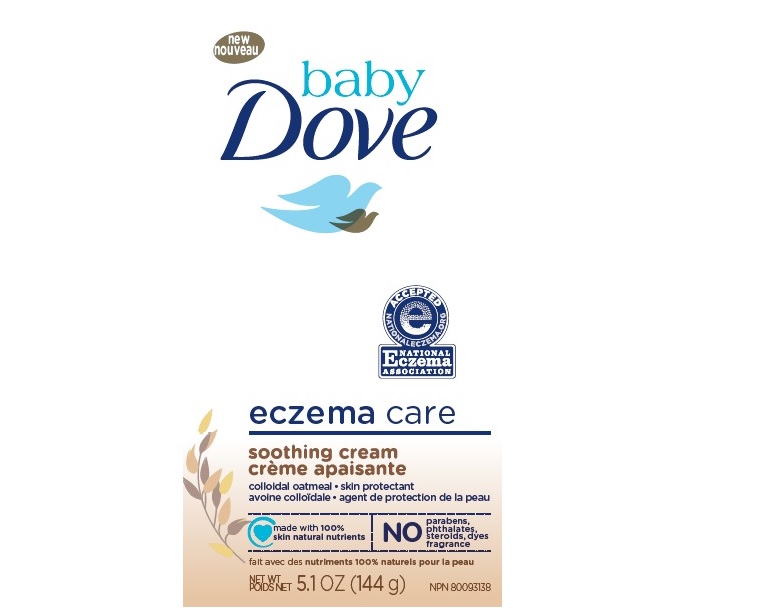 DRUG LABEL: Baby Dove
NDC: 64942-1873 | Form: CREAM
Manufacturer: Conopco, Inc. d/b/a/ Unilever
Category: otc | Type: HUMAN OTC DRUG LABEL
Date: 20241107

ACTIVE INGREDIENTS: OATMEAL 1 g/100 mL
INACTIVE INGREDIENTS: WATER; GLYCERIN; STEARIC ACID; ISOPROPYL PALMITATE; SHEA BUTTER; DIMETHICONE; AMMONIUM ACRYLOYLDIMETHYLTAURATE/VP COPOLYMER; CARNAUBA WAX; CETOSTEARYL ALCOHOL; PHENOXYETHANOL; GLYCERYL HYDROXYSTEARATE; DIMETHICONE CROSSPOLYMER (450000 MPA.S AT 12% IN CYCLOPENTASILOXANE); 12-HYDROXYSTEARIC ACID; CAPRYLYL GLYCOL; CETEARYL GLUCOSIDE; SODIUM CETOSTEARYL SULFATE; CETYL PALMITATE; SODIUM BENZOATE; EDETATE SODIUM

Baby Dove Eczema Care Soothing Cream

Description

BABY DOVE ECZEMA CARE SOOTHING CREAM - (colloidal oatmeal) cream

Drug Facts

Active ingredient
Colloidal Oatmeal (1%)

Purpose

Skin Protectant

Uses

temporarily protects and helps relieve minor skin irritation and itching due to:

- eczema

Warnings

For external use only
When using this product do not get into eyes.r.
Stop use and ask a doctor if

- condition worsens
- symptoms last more than 7 days or clear up and occur again within a few days

Keep out of reach of children. If product is swallowed, get medical help or contact a Poison Control Center right away.

Directions

Apply as needed

Other Information

Do not use if tamper evident seal is missing or broken.

Inactive ingredients

Water (Eau), Glycerin, Dimethicone, Butyrospermum Parkii (Shea) Butter, Copernicia Cerifera (Carnauba) Wax, Isopropyl Myristate, Cetearyl Alcohol, Glyceryl Hydroxystearate, Dimethicone Crosspolymer, Hydroxystearic Acid, Caprylyl Glycol, Cetearyl Glucoside, Sodium Cetearyl Sulfate, Cetyl Palmitate, Sodium Benzoate, Phenoxyethanol, Ammonium Acryloyldimethyltaurate/VP Copolymer, Stearic Acid, Tetrasodium EDTA.

Questions or comments?

1-800-761-3683